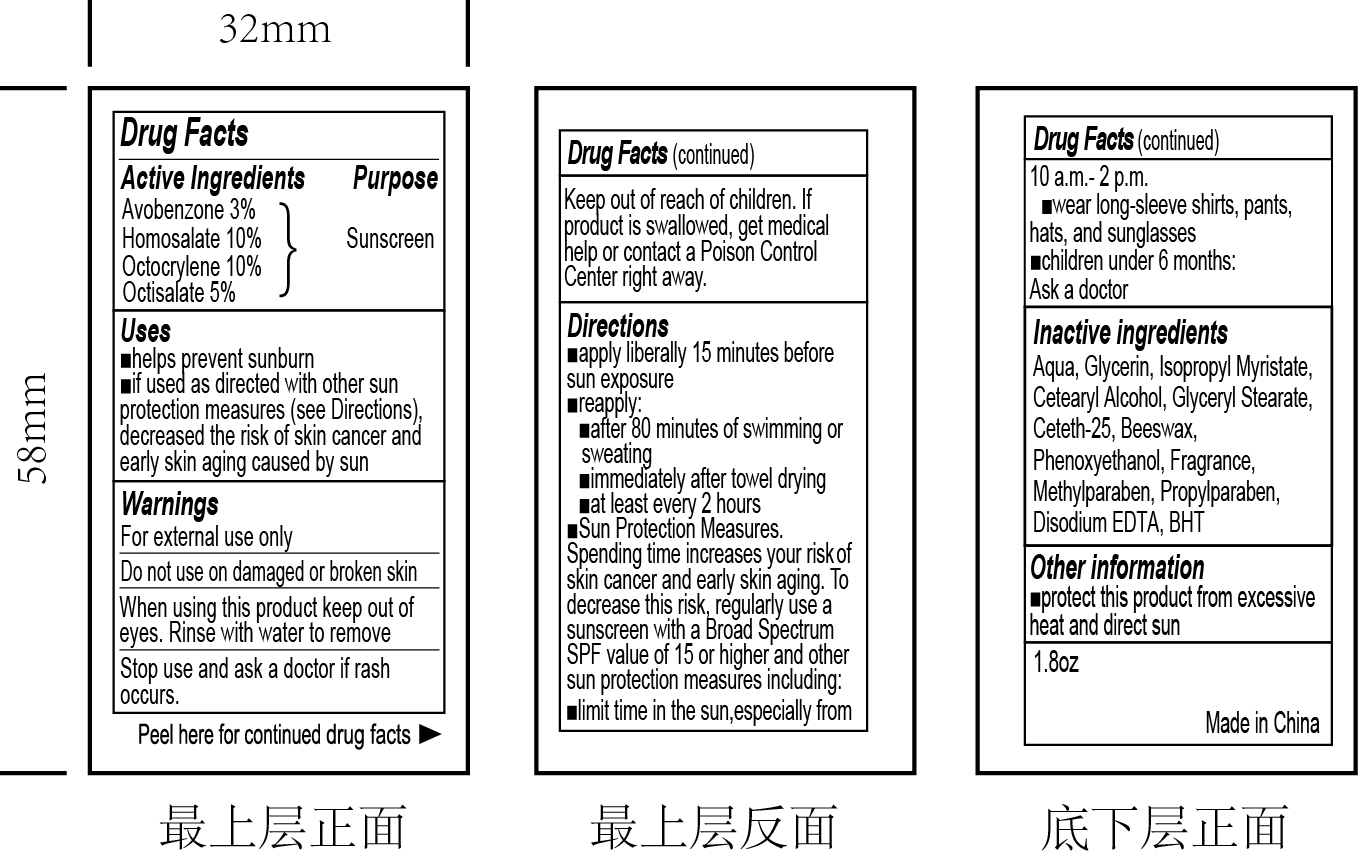 DRUG LABEL: SUNSCREEN
NDC: 82953-002 | Form: CREAM
Manufacturer: Cosmuses Cosmetics (Ningbo) Co., Ltd.
Category: otc | Type: HUMAN OTC DRUG LABEL
Date: 20241204

ACTIVE INGREDIENTS: OCTOCRYLENE 10 g/100 g; HOMOSALATE 10 g/100 g; AVOBENZONE 3 g/100 g; OCTISALATE 5 g/100 g
INACTIVE INGREDIENTS: WATER; GLYCERIN; PHENOXYETHANOL; YELLOW WAX; CETOSTEARYL ALCOHOL; CETETH-25; METHYLPARABEN; GLYCERYL STEARATE SE; EDETATE DISODIUM ANHYDROUS; ISOPROPYL MYRISTATE; PROPYLPARABEN; BUTYLATED HYDROXYTOLUENE

SPF30 SUNSCREEN LOTION

Drug Facts

Active ingredients

Avobenzone 3%

Homosalate 10%

Octocrylene 10%

Octisalate 5%

Purpose

Sunscreen

Uses

- Helps prevent sunburn
- If used as directed with other sun protection measures (see Directions), decreased the risk of skin cancer and early skin aging caused by sun.

Warnings

For external use only

Do not use on damaged or broken skin.

When using this product keep out of eyes. Rinse with water to remove.

Stop use and ask a doctor if rash occurs.

Keep out of reach of children. If prduct is swallowed, get medical help or contact a Poison Control Center right away.

Directions

- apply liberally 15minutes before sun exposure
- reapply:
- after 80 minutes of swimming or sweating
- immediate after towel drying
- at least every 2 hours
- Sun Protection Measures

Spending time increases your risk of skin cancer and early skin aging. To decreases this risk, regularly use a sunscreen with a Broad Spectrum SPF value of 15 or higher and other sun protection measures including:

- limit time in the sun, especially from 10a.m.- 2p.m.
- wear long-sleeve shirts, pants, hats and sunglasses
- children under 6 months

Ask a doctor

Inactive ingredients

Aqua, Glycerin, Isopropyl Myristate, Cetearyl Alcohol, Glyceryl Stearate, Ceteth-25, Beeswax, Phenoxyethanol, Fragrance, Methylparaben, Propylparaben, Disodium EDTA, BHT

Other information

Protect this product from excessive heat and direct sun